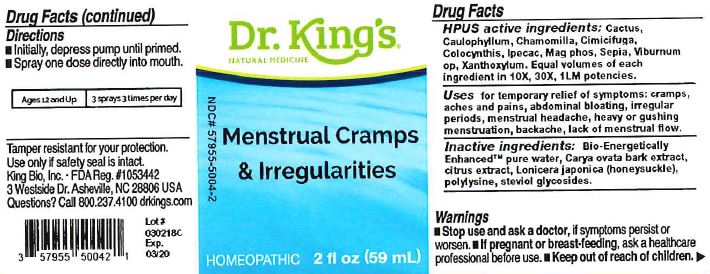 DRUG LABEL: Menstrual Cramps and Irregularities
NDC: 57955-5004 | Form: LIQUID
Manufacturer: King Bio Inc.
Category: homeopathic | Type: HUMAN OTC DRUG LABEL
Date: 20180410

ACTIVE INGREDIENTS: SELENICEREUS GRANDIFLORUS STEM 10 [hp_X]/59 mL; CAULOPHYLLUM THALICTROIDES ROOT 10 [hp_X]/59 mL; MATRICARIA RECUTITA 10 [hp_X]/59 mL; BLACK COHOSH 10 [hp_X]/59 mL; CITRULLUS COLOCYNTHIS FRUIT PULP 10 [hp_X]/59 mL; IPECAC 10 [hp_X]/59 mL; MAGNESIUM PHOSPHATE, DIBASIC TRIHYDRATE 10 [hp_X]/59 mL; SEPIA OFFICINALIS JUICE 10 [hp_X]/59 mL; VIBURNUM OPULUS BARK 10 [hp_X]/59 mL; ZANTHOXYLUM AMERICANUM BARK 10 [hp_X]/59 mL
INACTIVE INGREDIENTS: WATER; CARYA OVATA BARK; CITRUS BIOFLAVONOIDS; LONICERA JAPONICA FLOWER; POLYEPSILON-LYSINE (4000 MW); REBAUDIOSIDE A

Menstrual Cramps and Irregularities

ACTIVE INGREDIENT

Drug Facts__________________________________________________________________________________________________________

HPUS active ingredients: Cactus, Caulophyllum, Chamomilla, Cimicifuga, Colocynthis, Ipecac, Mag phos, Sepia, Viburnum op, Xanthoxylum. Equal volumes of each ingredient in 10X, 30X, 1LM potencies.

INDICATIONS AND USAGE

Uses for temporary relief of symptoms: cramps, aches and pains, abdominal bloating, irregular periods, menstrual headache, heavy or gushing menstruation, backache, lack of menstrual flow.

Inactive Ingredients:

Bio-Energetically Enhanced™ pure water, Carya ovata bark extract, citrus extract, Lonicera japonica (honeysuckle), polylysine, steviol glycosides.

Warnings

- Stop use and ask a doctor if symptoms persist or worsen.
- If pregnant or breast-feeding, ask a healthcare professional before use.

- Keep out of reach of children.

Directions

- Initially, depress pump until primed.
- Spray one dose directly into mouth.
- Ages 12 and up: 3 sprays 3 times per day.

OTHER SAFETY INFORMATION

Tamper resistant for your protection. Use only if safety seal is intact.

PURPOSE

Uses for temporary relief of symptoms:

- cramps
- aches and pains
- abdominal bloating
- irregular periods
- menstrual headache
- heavy or gushing menstruation,
- backache
- lack of menstrual flow